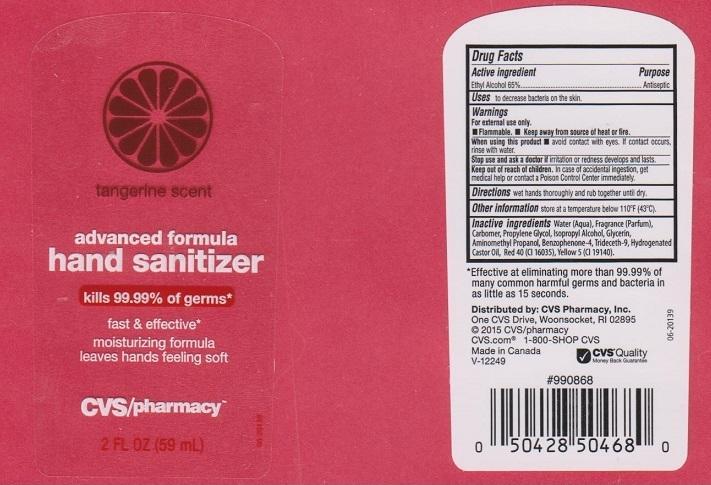 DRUG LABEL: CVS PHARMACY
NDC: 59779-156 | Form: LIQUID
Manufacturer: CVS PHARMACY
Category: otc | Type: HUMAN OTC DRUG LABEL
Date: 20150122

ACTIVE INGREDIENTS: ALCOHOL 650 mg/1 mL
INACTIVE INGREDIENTS: WATER; CARBOMER 934; PROPYLENE GLYCOL; ISOPROPYL ALCOHOL; GLYCERIN; AMINOMETHYLPROPANOL; SULISOBENZONE; TRIDECETH-9; HYDROGENATED CASTOR OIL; FD&C RED NO. 40; FD&C YELLOW NO. 5

DRUG FACTS

ACTIVE INGREDIENT

ETHYL ALCOHOL 65%

PURPOSE

ANTISEPTIC

USES

TO DECREASE BACTERIA ON THE SKIN

WARNINGS

FOR EXTERNAL USE ONLY. FLAMMABLE. KEEP AWAY FROM SOURCE OF HEAT OR FIRE

WHEN USING THIS PRODUCT

AVOID CONTACT WITH EYES. IF CONTACT OCCURS, RINSE WITH WATER

STOP USE AND ASK A DOCTOR IF

IRRITATION OR REDNESS DEVELOPS AND LASTS

KEEP OUT OF REACH OF CHILDREN

IN CASE OF ACCIDENTAL INGESTION, GET MEDICAL HELP OR CONTACT A POISON CONTROL CENTER IMMEDIATELY

DIRECTIONS

WET HANDS THOROUGHLY AND RUB TOGETHER UNTIL DRY

OTHER INFORMATION

STORE AT A TEMPERATURE BELOW 110°F (43°C)

INACTIVE INGREDIENTS

WATER (AQUA), FRAGRANCE (PARFUM), CARBOMER, PROPYLENE GLYCOL, ISOPROPYL ALCOHOL, GLYCERIN, AMINOMETHYL PROPANOL, BENZOPHENONE-4, TRIDECETH-9, HYDROGENATED CASTOR OIL, RED 40 (CI 16035), YELLOW 5 (CI 19140)